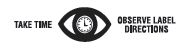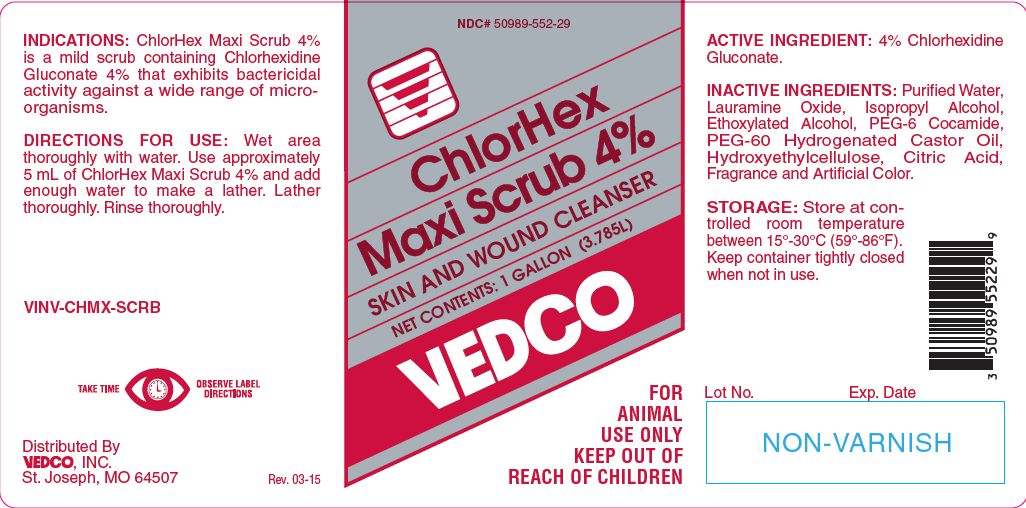 DRUG LABEL: ChlorHex Maxi Scrub
NDC: 50989-552 | Form: SOLUTION
Manufacturer: Vedco, Inc.
Category: animal | Type: OTC ANIMAL DRUG LABEL
Date: 20221111

ACTIVE INGREDIENTS: CHLORHEXIDINE GLUCONATE 214.5 g/1 L

ChlorHex Maxi Scrub 4%

PURPOSE

SKIN AND WOUND CLEANSER

KEEP OUT OF REACH OF CHILDREN

FOR ANIMAL USE ONLY
KEEP OUT OF REACH OF CHILDREN

INDICATIONS:

ChlorHex Maxi Scrub 4% is a mild scrub containing Chlorhexidine Gluconate 4% that exhibits bactericidal activity against a wide range of microorganisms.

DIRECTIONS FOR USE:

Wet area thoroughly with water. Use approximately 5 mL of ChlorHex Maxi Scrub 4% and add enough water to make a lather. Lather thoroughly. Rinse thoroughly.

ACTIVE INGREDIENT:

4% Chlorhexidine Gluconate.

INACTIVE INGREDIENTS:

Purified Water, Lauramine Oxide, Isopropyl Alcohol, Ethoxylated Alcohol, PEG-6 Cocamide, PEG-60 Hydrogenated Castor Oil, Hydroxyethylcellulose, Citric Acid, Fragrance and Artificial Color.

STORAGE:

Store at controlled room temperature between 15°-30°C (59°-86°F). Keep container tightly closed when not in use.

NET CONTENTS:

1 GALLON (3.785L)

INFORMATION FOR OWNERS/CAREGIVERS

VINV-CHMX-SCRB

Distributed By
VEDCO, INC.
St. Joseph, MO 64507